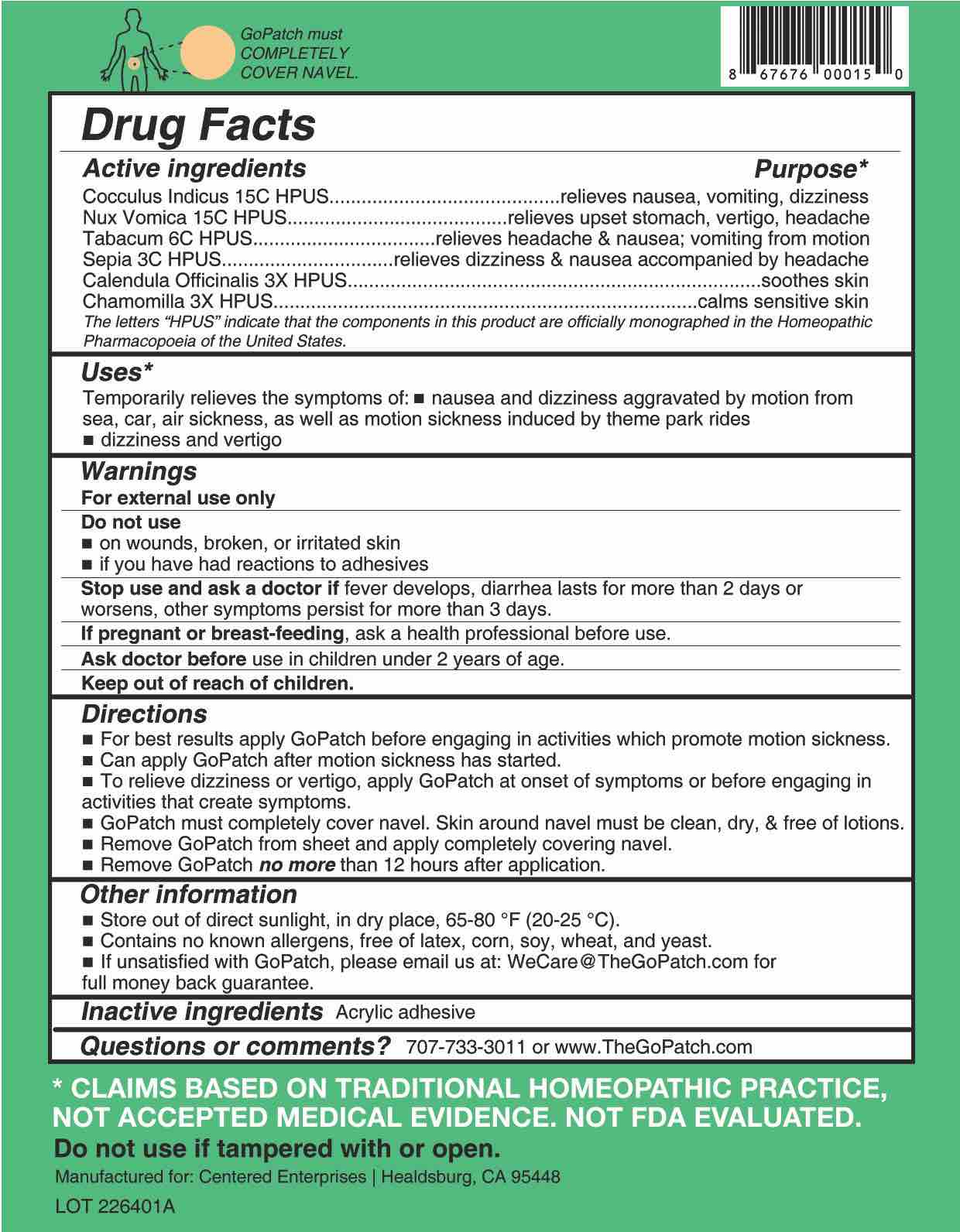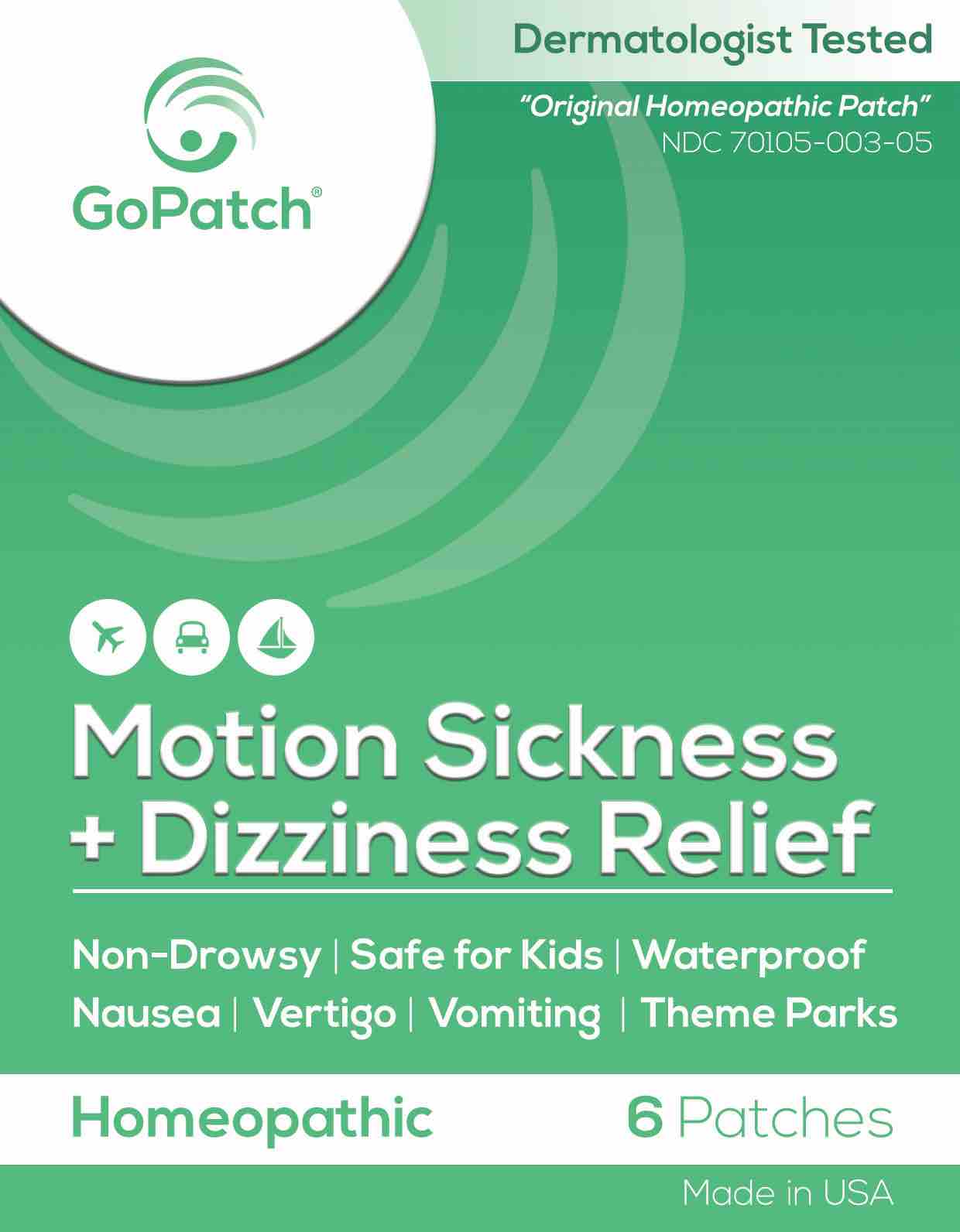 DRUG LABEL: GoPatch Motion Sickness and Dizziness Relief
NDC: 70105-003 | Form: PATCH
Manufacturer: Centered Enterprises, LLC
Category: homeopathic | Type: HUMAN OTC DRUG LABEL
Date: 20240115

ACTIVE INGREDIENTS: CALENDULA OFFICINALIS FLOWERING TOP 3 [hp_X]/1 1; MATRICARIA RECUTITA 3 [hp_X]/1 1; SEPIA OFFICINALIS JUICE 3 [hp_C]/1 1; TOBACCO LEAF 6 [hp_C]/1 1; ANAMIRTA COCCULUS SEED 15 [hp_C]/1 1; STRYCHNOS NUX-VOMICA SEED 15 [hp_C]/1 1
INACTIVE INGREDIENTS: POLYVINYL ACETATE; WATER; ALCOHOL

GoPatch Motion Sickness and Dizziness Relief

Active ingredients | Purpose*
Cocculus Indicus 15C HPUS | relieves nausea, vomiting, dizziness
Nux Vomica 15C HPUS | relieves upset stomach, vertigo, headache
Tabacum 6C HPUS | relieves headache & nausea; vomiting from motion
Sepia 3C HPUS | relieves dizziness & nausea accompanied by headache
Calendula Officinalis 3X HPUS | soothes skin
Chamomilla 3X HPUS | calms sensitive skin

The letters "HPUS" indicate that the components in this product are officially monographed in the Homeopathic Pharmacopoeia of the United States.

Purpose*

Cocculus Indicus - relieves nausea, vomiting, dizziness

Nux Vomica - relieves upset stomach, vertigo, headache

Tabacum - relieves headache & nausea; vomiting from motion

Sepia - relieves dizziness & nausea accompanied by headache

Calendula Officinalis - soothes skin

Chamomilla - calms sensitive skin

Uses

Temporarily relieves the symptoms of: ■ nausea and dizziness aggravated by motion from sea, car, air sickness, as well as motion sickness induced by theme park rides.

■ dizziness and vertigo

Warnings

- For external use only.

Do Not Use

■ on wounds, broken, or irritated skin
■ if you have had reactions to adhesives

Stop Use

Stop use and ask a doctor if fever develops, diarrhea lasts for more than 2 days or worsens, other symptoms persist for more than 3 days.

If pregnant or breast-feeding, ask a health professional before use.

Ask Doctor

Ask doctor before use in children under 2 years of age.

- Keep out of reach of children.

Directions

■ For best results apply GoPatch efore engaging in activities which promote motion sickness.

■ Can apply GoPatch after motion sickness has started.

■ To relieve dizziness or vertigo, apply GoPatch at onset of symptoms or before engaging in activities that create symptoms.

■ GoPatch must completely cover the navel. Skin around navel must be clean, dry & free of lotions.
■ Remove GoPatch from sheet and apply completely covering navel.
■ Remove GoPatch no more than 12 hours after application.

Other information

- Store out of direct sunlight, in dry place, at 65-80°F (20-25°C).
- Contains no known allergens, free of latex, corn, soy, wheat, and yeast.
- If unsatisfied with GoPatch, please email us at WeCare@TheGoPatch.com for full money back guarantee.

Inactive ingredients Acrylic adhesive

Questions?

Questions or comments? Please call us at (707) 733-3011 or www.TheGoPatch.com

PACKAGE LABEL

GoPatch™

NDC 70105-003-05

Homeopathic